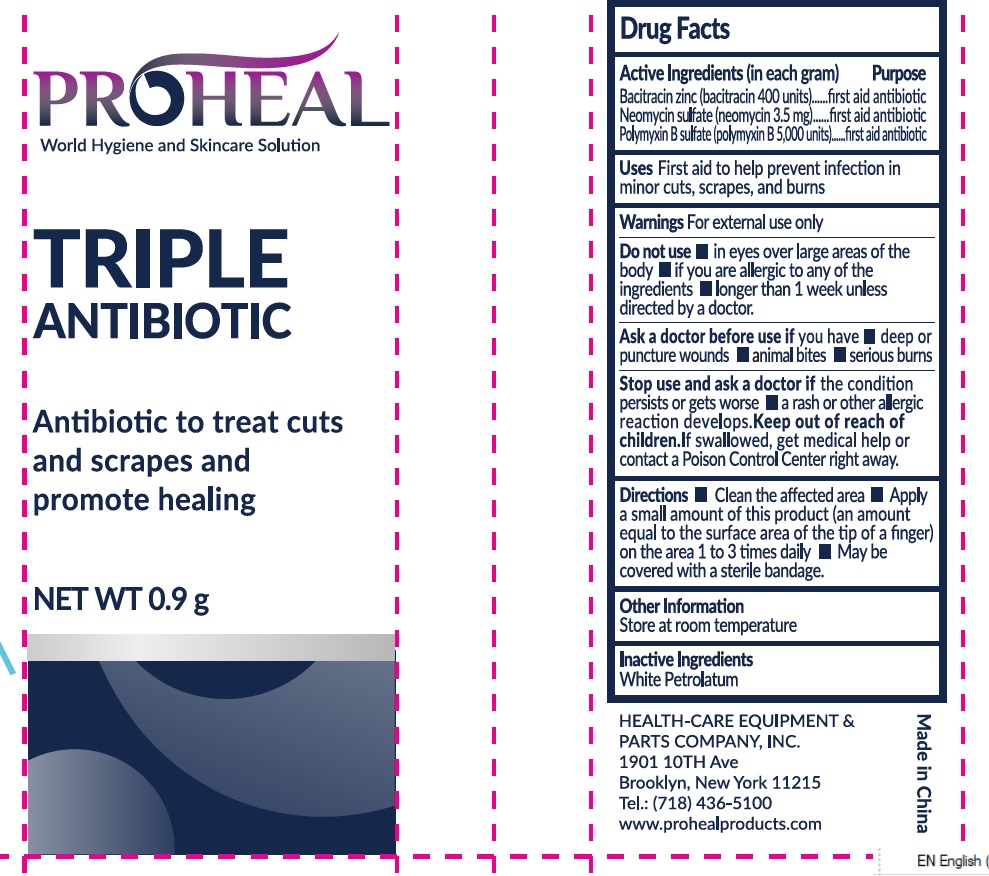 DRUG LABEL: PROHEAL TRIPLE ANTIBIOTIC
NDC: 43473-067 | Form: OINTMENT
Manufacturer: Nantong Health & Beyond Hygienic Products Inc.
Category: otc | Type: HUMAN OTC DRUG LABEL
Date: 20250813

ACTIVE INGREDIENTS: BACITRACIN ZINC 400 [USP'U]/1 g; NEOMYCIN SULFATE 0.0035 g/1 g; POLYMYXIN B SULFATE 5000 [USP'U]/1 g
INACTIVE INGREDIENTS: PETROLATUM

43473-067, PROHEAL tri antibiotics

Active Ingredients (in each gram)

Bacitracin zinc (bacitracin 400 units)
Neomycin sulfate (neomycin 3.5 mg)
Polymyxin B sulfate (polymyxin B 5.000 units

Purpose

First aid antibiotic

First aid antibiotic

First aid antibiotic

Uses

First aid to help prevent infection in minor cuts, scrapes and burns

Warnings

For external use only.

Do not use

- in the eyes
- over large areas of the body
- if you are allergic to any of the ingredients
- longer than 1 week unless directed by a doctor.

Ask a doctor before use if you have

- deep or puncture wounds
- animal bites
- serious burns

Stop use and ask a doctor if

- if the condition persists or gets worse
- a rash or other allergic reaction develops.

Keep out of reach of children

If swallowed, get medical help or contact a Poison Control Center right away

Directions

- Clean and disinfect the affected area
- Apply a small amount of this product (an amount equal to the surface area of the tip of a finger) on the area 1 to 3 times daily
- May be covered with a sterile bandage.

Other Information

Store at room temperature

Inactive Ingredients

White petrolatum